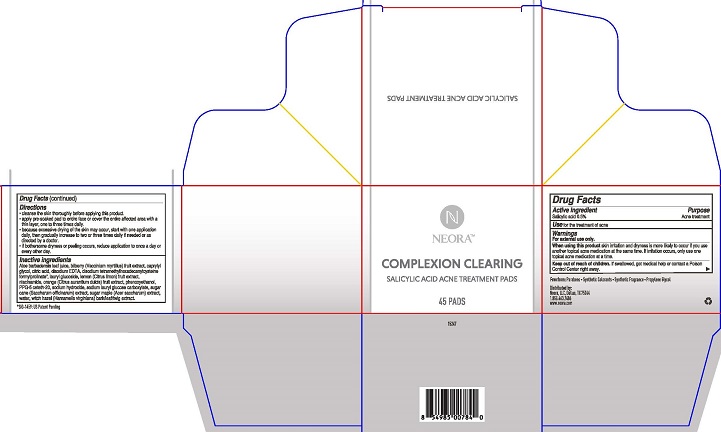 DRUG LABEL: Neora
NDC: 72935-001 | Form: SWAB
Manufacturer: Neora, LLC
Category: otc | Type: HUMAN OTC DRUG LABEL
Date: 20231023

ACTIVE INGREDIENTS: SALICYLIC ACID 0.5 g/100 mL
INACTIVE INGREDIENTS: ALOE VERA LEAF; CAPRYLYL GLYCOL; CITRIC ACID MONOHYDRATE; EDETATE DISODIUM; LAURYL GLUCOSIDE; CITRUS LIMON FRUIT OIL; NIACINAMIDE; CITRUS AURANTIUM FRUIT OIL; PHENOXYETHANOL; PPG-5-CETETH-20; SODIUM HYDROXIDE; SODIUM LAURYL GLYCOL CARBOXYLATE; SACCHARUM OFFICINARUM WHOLE; ACER SACCHARUM SAP; WATER; WITCH HAZEL; BILBERRY

Neora Complexion Clearing Acne Treatment Pads

Drug Facts

Active ingredient

Salicylic acid 0.5%

Purpose

Acne treatment

Use

for the treatment of acne

Warnings

For external use only.

When using this product skin irritation and dryness is more likely to occur if you use another topical acne medication at the same time. If irritation occurs, only use one topical acne medication at a time.

Keep out of reach of children. If swallowed, get medical help or contact a Poison Control Center right away.

Directions

- cleanse the skin thoroughly before applying this product.
- apply pre-soaked pad to entire face or cover the entire affected area with a thin layer, one to three times daily.
- because excessive drying of the skin may occur, start with one application daily, then gradually increase to two or three times daily if needed or as directed by a doctor.
- if bothersome dryness or peeling occurs, reduce application to once a day or every other day.

INACTIVE INGREDIENT

Inactive ingredients Aloe barbadensis leaf juice, bilberry (Vaccinium myrtillus) fruit extract, caprylyl glycol, citric acid, disodium EDTA, disodium tetramethylhexadecenylcysteine formylprolinate, lauryl glucoside, lemon (Citrus limon) fruit extract, niacinamide, orange (Citrus aurantium dulcis) fruit extract, phenoxyethanol, PPG-5 ceteth-20, sodium hydroxide, sodium lauryl glucose carboxylate, sugar cane (Saccharum officinarum) extract, sugar maple (Acer saccharum) extract, water, witch hazel (Hamamelis virginiana) bark/leaf/twig extract.

Free from: Parabens • Synthetic Colorants • Synthetic Fragrance • Propylene Glycol

Distributed by:

Neora, LLC, Dallas, TX 75244

1.855.463.7486

www.neora.com

PACKAGE LABEL

NEORA™

COMPLEXION CLEARING

SALICYLIC ACID ACNE TREATMENT PADS

45 PADS